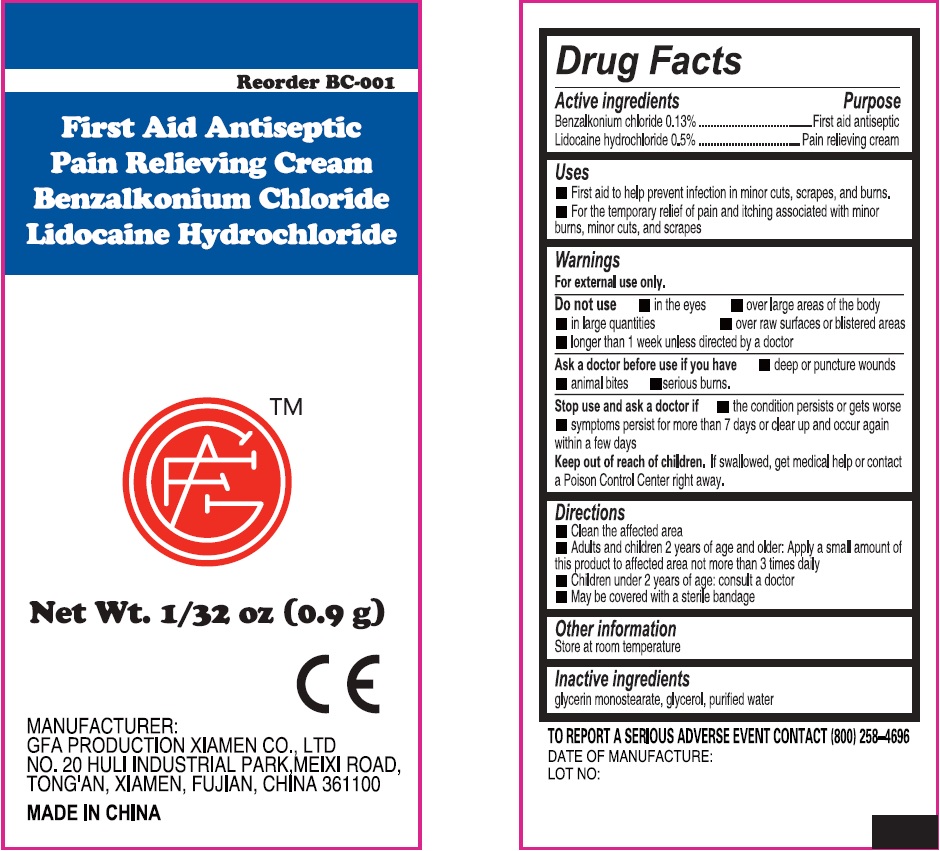 DRUG LABEL: First Aid Antiseptic Pain Relieving
NDC: 50814-009 | Form: CREAM
Manufacturer: GFA Production (Xiamen) Co., Ltd.
Category: otc | Type: HUMAN OTC DRUG LABEL
Date: 20250430

ACTIVE INGREDIENTS: BENZALKONIUM CHLORIDE 1.3 mg/1 g; LIDOCAINE HYDROCHLORIDE 5 mg/1 g
INACTIVE INGREDIENTS: GLYCERIN; WATER

First Aid Antiseptic Pain Relieving Cream

Active ingredients

Benzalkonium chloride 0.13%

Lidocaine hydrochloride 0.5

Purpose

First aid antiseptic

Pain relieving cream

Uses

- First aid to help prevent infection in minor cuts, scrapes, and burns.
- For the temporary relief of pain and itching associated with minor burns, minor cuts, and scrapes.

Warnings

For external use only.

Do not use

• in the eyes • over large areas of the body • in large quantities • over raw surfaces or blistered areas • longer than 1 week unless directed by a doctor

Ask a doctor before use if you have

• deep or puncture wounds • animal bites • serious burns.

Stop use and ask a doctor if

• the condition persists or gets worse • symptoms persist for more than 7 days or clear up and occur again within a few days

Keep out of reach of children.

If swallowed, get medical help or contact a Poison Control Center right away.

Directions

- Clean the affected area
- Adults and children 2 years of age and older: Apply a small amount of this product to affected area not more than 3 times daily
- Children under 2 years of age: consult a doctor
- May be covered with a sterile bandage

Other information

Store at room temperature

Inactive ingredients

glycerin monostearate, glycerol, purified water